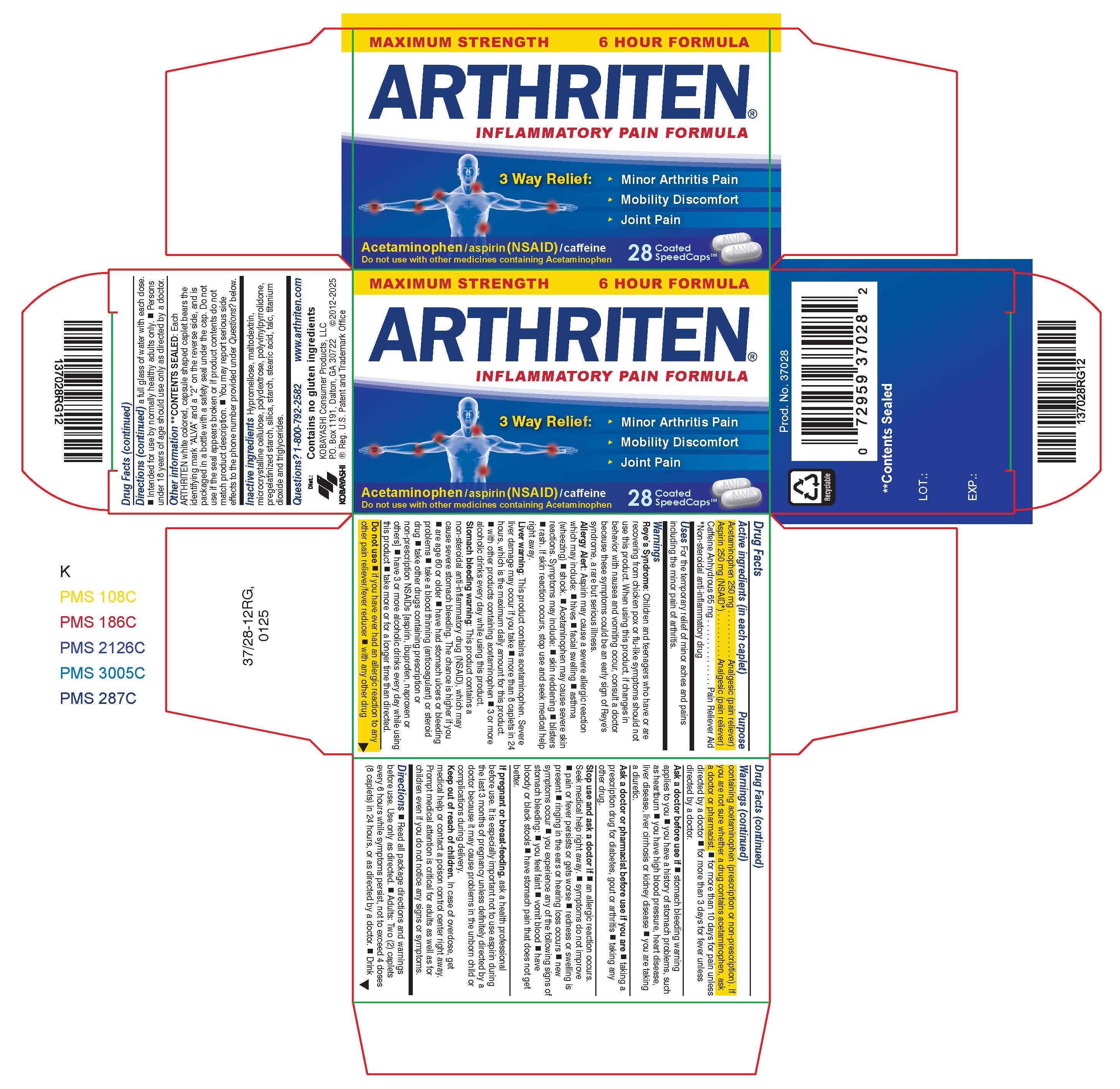 DRUG LABEL: Arthriten
NDC: 52389-237 | Form: TABLET, FILM COATED
Manufacturer: Kobayashi Healthcare International, Inc
Category: otc | Type: HUMAN OTC DRUG LABEL
Date: 20250411

ACTIVE INGREDIENTS: ACETAMINOPHEN 250 mg/1 1; CAFFEINE 65 mg/1 1; ASPIRIN 250 mg/1 1
INACTIVE INGREDIENTS: MALTODEXTRIN; CELLULOSE, MICROCRYSTALLINE; POLYDEXTROSE; POVIDONE K30; STARCH, CORN; SILICON DIOXIDE; STEARIC ACID; TALC; TITANIUM DIOXIDE; MEDIUM-CHAIN TRIGLYCERIDES; HYPROMELLOSES

Arthriten Inflammatory Pain Formula

Active ingredients (in each caplet)

Acetaminophen, 250 mg

Aspirin, 250 mg (NSAID)*

Caffeine Anhydrous, 65 mg

*Non-steroidal anti-inflammatory drug

Purpose

Analgesic (pain reliever)

Analgesic (pain reliever)

Pain Reliever Aid

INDICATIONS AND USAGE

Uses For the temporary relief of minor aches and pains including the minor pain of arthritis.

Warnings

Reye's Syndrome: Children and teenagers who have or are recovering from chicken pox or flu-like symptoms should not use this product. When using this product, if changes in behavior with nausea and vomiting occur, consult a doctor because these symptoms could be an early sign of Reye's Syndrome, a rare but serious illness.

Allergy alert:

Aspirin may cause a severe allergic reaction which may include:

- hives
- facial swelling
- asthma (wheezing)
- shock

Acetaminophen may cause severe skin reactions. Symptoms may include:

- skin reddening
- blisters
- rash

If skin reaction occurs, stop use and seek medical help right away.

Liver warning: This product contains acetaminophen. Severe liver damage may occur if you take

- more than 8 caplets in 24 hours, which is the maximum daily amount for this product.
- with other products containing acetaminophen
- 3 or more alcoholic drinks every day while using this product.

Stomach bleeding warning: This product contains a non-steroidal anti-inflammatory drug (NSAID), which may cause severe stomach bleeding. The chance is higher if you

- are age 60 or older
- have had stomach ulcers or bleeding problems
- take a blood thinning (anti-coagulant) or steroid drug
- take other drugs containing prescription or nonprescription NSAIDs [aspirin, ibuprofen, naproxen or others]
- have 3 or more alcoholic drinks every day while using this product
- take more or for a longer time than directed.

Do not use

- if you have ever had an allergic reaction to any other pain reliever/fever reducer
- with any other drug containing acetaminophen (prescription or non-prescription). If you are not sure whether a drug contains acetaminophen, ask a doctor or pharmacist.
- for more than 10 days for pain unless directed by a doctor
- for more than 3 days for fever unless directed by a doctor.

Ask a doctor before use if

- stomach bleeding warning applies to you
- you have a history of stomach problems, such as heartburn
- you have high blood pressure, heart disease, liver disease, liver cirrhosis or kidney disease
- you are taking a diuretic

Ask a doctor or pharmacist before use if you are

- taking a prescription drug for diabetes, gout or arthritis
- taking any other drug.

Stop use and ask a doctor if

- an allergic reaction occurs. Seek medical help right away.
- symptoms do not improve
- pain or fever persists or gets worse
- redness or swelling is present.
- ringing in the ears or hearing loss occurs.
- new symptoms occur
- you experience any of the following signs of stomach bleeding:
-
  - you feel faint
  - vomit blood
  - have bloody or black stools
  - have stomach pain that does not get better

PREGNANCY OR BREAST FEEDING

If pregnant or breastfeeding, ask a health professional before use. It is especially important not to use aspirin during the last 3 months of pregnancy unless definitely directed by a doctor because it may cause problems in the unborn child or complications during delivery.

Keep out of reach of children. In case of overdose, get medical help or contact a poison control center right away. Prompt medical attention is critical for adults as well as for children even if you do not notice any signs or symptoms.

Directions

- Read all package directions and warnings before use and use only as directed.
- Adults: Two (2) caplets every 6 hours while symptoms persist, not to exceed 4 doses (8 caplets) in 24 hours, or as directed by a doctor.
- Drink a full glass of water with each dose
- Intended for use by normally healthy adults only
- Persons under 18 years of age should use only as directed by a doctor.

Other information

**Contents sealed: Each Arthriten white colored, capsule shaped caplet bears the identifying mark "ALVA" and a "2" on the reverse side, and is packaged in a bottle with a safety seal under the cap. Do not use if the seal appears broken or if product contents do not match product description. You may report serious side effects to the phone number provided under Questions? below.

INACTIVE INGREDIENT

Inactive ingredients: Hypromellose, maltodextrin, microcrystalline cellulose, polydextrose, polyvinylpyrrolidone, pregelatinized starch, silica, starch, stearic acid, talc, titanium dioxide and triglycerides.

Questions? 1-800-792-2582